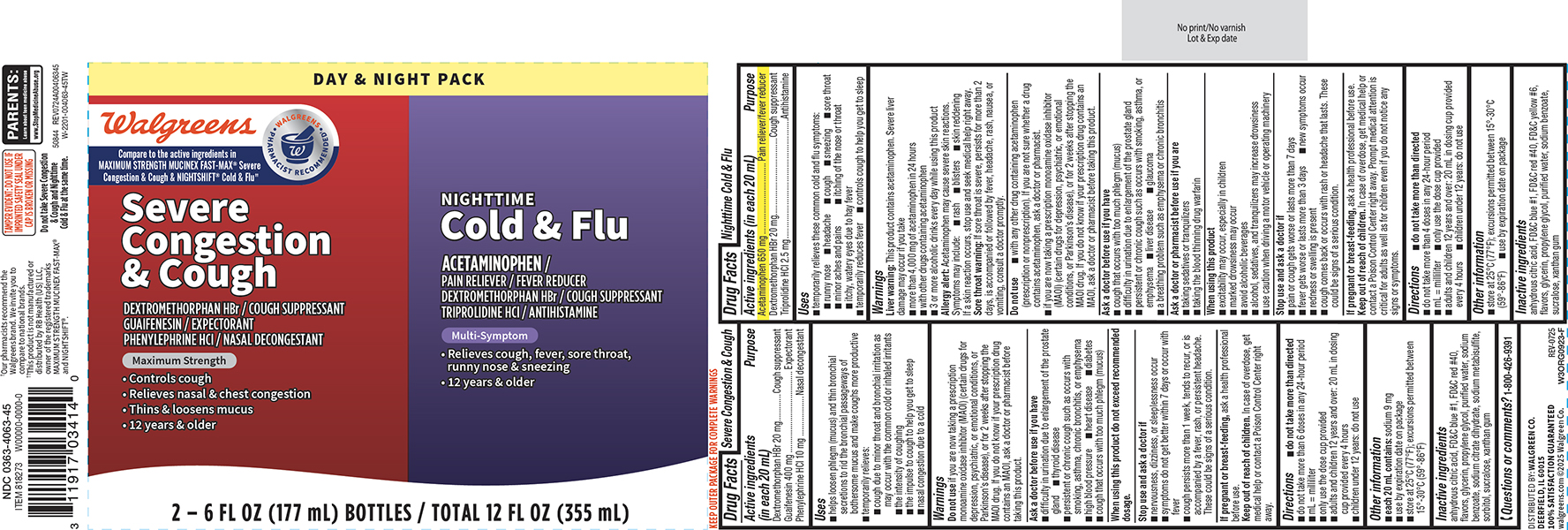 DRUG LABEL: Severe Congestion and Cough, Cold and Flu
NDC: 0363-4063 | Form: KIT | Route: ORAL
Manufacturer: Walgreen Company
Category: otc | Type: HUMAN OTC DRUG LABEL
Date: 20251216

ACTIVE INGREDIENTS: DEXTROMETHORPHAN HYDROBROMIDE 20 mg/20 mL; GUAIFENESIN 400 mg/20 mL; PHENYLEPHRINE HYDROCHLORIDE 10 mg/20 mL; ACETAMINOPHEN 650 mg/20 mL; DEXTROMETHORPHAN HYDROBROMIDE 20 mg/20 mL; TRIPROLIDINE HYDROCHLORIDE 2.5 mg/20 mL
INACTIVE INGREDIENTS: ANHYDROUS CITRIC ACID; FD&C BLUE NO. 1; FD&C RED NO. 40; GLYCERIN; PROPYLENE GLYCOL; WATER; SODIUM BENZOATE; TRISODIUM CITRATE DIHYDRATE; SODIUM METABISULFITE; SORBITOL; SUCRALOSE; XANTHAN GUM; ANHYDROUS CITRIC ACID; FD&C BLUE NO. 1; FD&C RED NO. 40; FD&C YELLOW NO. 6; GLYCERIN; PROPYLENE GLYCOL; WATER; SODIUM BENZOATE; SUCRALOSE; XANTHAN GUM

Walgreens 44-004063-45

Severe Congestion & Cough

Active ingredients (in each 20 mL)

Dextromethorphan HBr 20 mg
Guaifenesin 400 mg
Phenylephrine HCl 10 mg

Purpose

Cough suppressant
Expectorant
Nasal decongestant

Uses

- helps loosen phlegm (mucus) and thin bronchial secretions to rid the bronchial passageways of bothersome mucus and make coughs more productive
- temporarily relieves:
  - cough due to minor throat and bronchial irritation as may occur with the common cold or inhaled irritants
  - the intensity of coughing
  - the impulse to cough to help you get to sleep
  - nasal congestion due to a cold

Warnings

Do not use

if you are now taking a prescription monoamine oxidase inhibitor (MAOI) (certain drugs for depression, psychiatric, or emotional conditions, or Parkinson’s disease), or for 2 weeks after stopping the MAOI drug. If you do not know if your prescription drug contains an MAOI, ask a doctor or pharmacist before taking this product.

Ask a doctor before use if you have

- difficulty in urination due to enlargement of the prostate gland
- thyroid disease
- persistent or chronic cough such as occurs with smoking, asthma, chronic bronchitis, or emphysema
- high blood pressure
- heart disease
- diabetes
- cough that occurs with too much phlegm (mucus)

When using this product

do not exceed recommended dosage.

Stop use and ask a doctor if

- nervousness, dizziness, or sleeplessness occur
- symptoms do not get better within 7 days or occur with fever
- cough persists more than 1 week, tends to recur, or is accompanied by a fever, rash, or persistent headache. These could be signs of a serious condition.

If pregnant or breast-feeding,

ask a health professional before use.

Keep out of reach of children.

In case of overdose, get medical help or contact a Poison Control Center right away.

Directions

- do not take more than directed
- do not take more than 6 doses in any 24-hour period
- mL = milliliter
- only use the dose cup provided
- adults and children 12 years and over: 20 mL in dosing cup provided every 4 hours
- children under 12 years: do not use

Other information

- each 20 mL contains: sodium 9 mg
- use by expiration date on package
- store at 25°C (77°F); excursions permitted between 15°-30°C (59°-86°F)

Inactive ingredients

anhydrous citric acid, FD&C blue #1, FD&C red #40, flavors, glycerin, propylene glycol, purified water, sodium benzoate, sodium citrate dihydrate, sodium metabisulfite, sorbitol, sucralose, xanthan gum

Questions or comments?

1-800-426-9391

Nighttime Cold & Flu

Active ingredients (in each 20 mL)

Acetaminophen 650 mg
Dextromethorphan HBr 20 mg
Triprolidine HCl 2.5 mg

Purpose

Pain reliever/fever reducer
Cough suppressant
Antihistamine

Uses

- temporarily relieves these common cold and flu symptoms:
  - runny nose
  - headache
  - cough
  - sneezing
  - sore throat
  - minor aches and pains
  - itching of the nose or throat
  - itchy, watery eyes due to hay fever
- temporarily reduces fever
- controls cough to help you get to sleep

Warnings

Liver warning: This product contains acetaminophen. Severe liver damage may occur if you take

- more than 4,000 mg of acetaminophen in 24 hours
- with other drugs containing acetaminophen
- 3 or more alcoholic drinks every day while using this product

Allergy alert: Acetaminophen may cause severe skin reactions. Symptoms may include:

- rash
- blisters
- skin reddening

If a skin reaction occurs, stop use and seek medical help right away.

Sore throat warning: If sore throat is severe, persists for more than 2 days, is accompanied or followed by fever, headache, rash, nausea, or vomiting, consult a doctor promptly.

Do not use

- with any other drug containing acetaminophen (prescription or nonprescription). If you are not sure whether a drug contains acetaminophen, ask a doctor or pharmacist.
- if you are now taking a prescription monoamine oxidase inhibitor (MAOI) (certain drugs for depression, psychiatric, or emotional conditions, or Parkinson’s disease), or for 2 weeks after stopping the MAOI drug. If you do not know if your prescription drug contains an MAOI, ask a doctor or pharmacist before taking this product.

Ask a doctor before use if you have

- cough that occurs with too much phlegm (mucus)
- difficulty in urination due to enlargement of the prostate gland
- persistent or chronic cough such as occurs with smoking, asthma, or emphysema
- liver disease
- glaucoma
- a breathing problem such as emphysema or chronic bronchitis

Ask a doctor or pharmacist before use if you are

- taking sedatives or tranquilizers
- taking the blood thinning drug warfarin

When using this product

- excitability may occur, especially in children
- marked drowsiness may occur
- avoid alcoholic beverages
- alcohol, sedatives, and tranquilizers may increase drowsiness
- use caution when driving a motor vehicle or operating machinery

Stop use and ask a doctor if

- pain or cough gets worse or lasts more than 7 days
- fever gets worse or lasts more than 3 days
- new symptoms occur
- redness or swelling is present
- cough comes back or occurs with rash or headache that lasts. These could be signs of a serious condition.

If pregnant or breast-feeding,

ask a health professional before use.

Keep out of reach of children.

In case of overdose, get medical help or contact a Poison Control Center right away. Prompt medical attention is critical for adults as well as for children even if you do not notice any signs or symptoms.

Directions

- do not take more than directed
- do not take more than 4 doses in any 24-hour period
- mL = milliliter
- only use the dose cup provided
- adults and children 12 years and over: 20 mL in dosing cup provided every 4 hours
- children under 12 years: do not use

Other information

- store at 25°C (77°F); excursions permitted between 15°-30°C (59°-86°F)
- use by expiration date on package

Inactive ingredients

anhydrous citric acid, FD&C blue #1, FD&C red #40, FD&C yellow #6, flavors, glycerin, propylene glycol, purified water, sodium benzoate, sucralose, xanthan gum

Principal Display Panel

NDC 0363-4063-45

DAY & NIGHT PACK

Walgreens

• WALGREENS •
PHARMACIST RECOMMENDED†

Compare to the active ingredients in
MAXIMUM STRENGTH MUCINEX FAST-MAX® Severe
Congestion & Cough & NIGHTSHIFT® Cold & Flu††

Severe
Congestion
& Cough
DEXTROMETHORPHAN HBr / COUGH SUPPRESSANT
GUAIFENESIN / EXPECTORANT
PHENYLEPHRINE HCl / NASAL DECONGESTANT

Maximum Strength

• Controls cough
• Relieves nasal & chest congestion
• Thins & loosens mucus
• 12 years & older

NIGHTTIME
Cold & Flu
ACETAMINOPHEN /
PAIN RELIEVER / FEVER REDUCER
DEXTROMETHORPHAN HBr / COUGH SUPPRESSANT
TRIPROLIDINE HCl / ANTIHISTAMINE

Multi-Symptom

• Relieves cough, fever, sore throat,
runny nose & sneezing
• 12 years & older

2 – 6 FL OZ (177 mL) BOTTLES / TOTAL 12 FL OZ (355 mL)

TAMPER EVIDENT: DO NOT USE IF
IMPRINTED SAFETY SEAL UNDER
CAP IS BROKEN OR MISSING

PARENTS:
Learn about teen medicine abuse
www.StopMedicineAbuse.org

Do not take Severe Congestion
& Cough and Nighttime
Cold & Flu at the same time.

50844 REV0724A00406345

†Our pharmacists recommend the
Walgreens brand. We invite you to
compare to national brands.

††This product is not manufactured or
distributed by RB Health (US) LLC,
owner of the registered trademarks
MAXIMUM STRENGTH MUCINEX FAST-MAX®
and NIGHTSHIFT®.

DISTRIBUTED BY: WALGREEN CO.
DEERFIELD, IL 60015
100% SATISFACTION GUARANTEED
walgreens.com ©2025 Walgreen Co.

Walgreens 44-004063